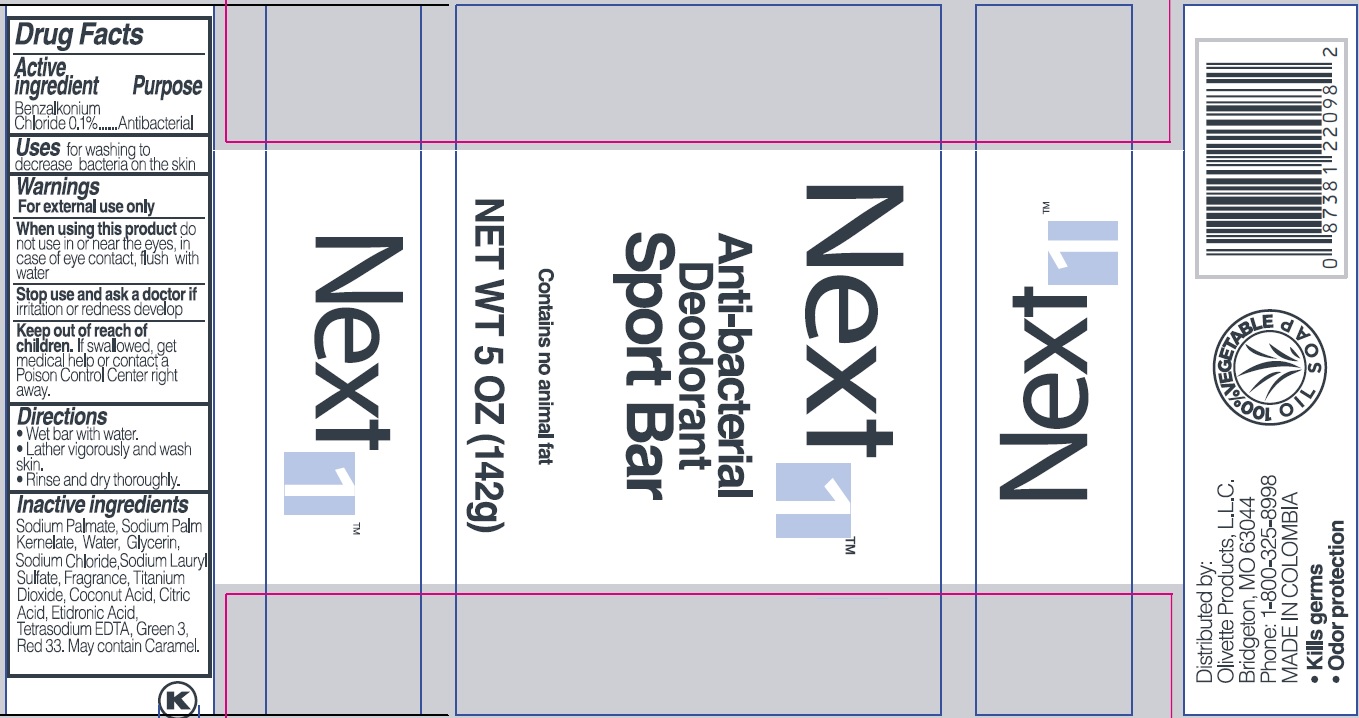 DRUG LABEL: Next1 Anti-bacterial Deodorant Sport
NDC: 51870-003 | Form: SOAP
Manufacturer: Keefe Group
Category: otc | Type: HUMAN OTC DRUG LABEL
Date: 20240101

ACTIVE INGREDIENTS: BENZALKONIUM CHLORIDE 0.1 g/100 g
INACTIVE INGREDIENTS: WATER; SODIUM PALMATE; SODIUM PALM KERNELATE; GLYCERIN; CARAMEL; SODIUM CHLORIDE; SODIUM LAURYL SULFATE; TITANIUM DIOXIDE; COCONUT ACID; CITRIC ACID MONOHYDRATE; ETIDRONIC ACID; EDETATE SODIUM; FD&C GREEN NO. 3; D&C RED NO. 33

Next1TM Anti-bacterial Deodorant Sport Bar

Drug Facts

Active ingredient

Benzalkonium Chloride 0.1%

Purpose

Antibacterial

INDICATIONS AND USAGE

Uses for washing to decrease bacteria on the skin

Warnings

For external use only

When using this product do not use in or near the eyes, in case of eye contact, flush with water

Stop use and ask a doctor if irritation or redness develop

Keep out of reach of children. If swallowed, get medical help or contact a Poison Control Center right away

Directions

- Wet bar with water.
- Lather vigorously and wash skin.
- Rinse and dry thoroughly.

INACTIVE INGREDIENT

Inactive ingredients Sodium Palmate, Sodium Palm Kernelate, Water, Glycerin, Sodium Chloride, Sodium Lauryl Sulfate, Fragrance, Titanium Dioxide, Coconut Acid, Citric Acid, Etidronic Acid, Tetrasodium EDTA, Green 3, Red 33. May contain Caramel.

Distributed by:

Olivette Products, L.L.C.

Bridgeton, MO 63044

Phone: 1-800-325-8998

MADE IN COLOMBIA

- Kills germs
- Odor protection

PACKAGE LABEL

Next 1TM

Anti-bacterial

Deodorant

Sport Bar

Contains no animal fat

NET WT 5 OZ (142g)